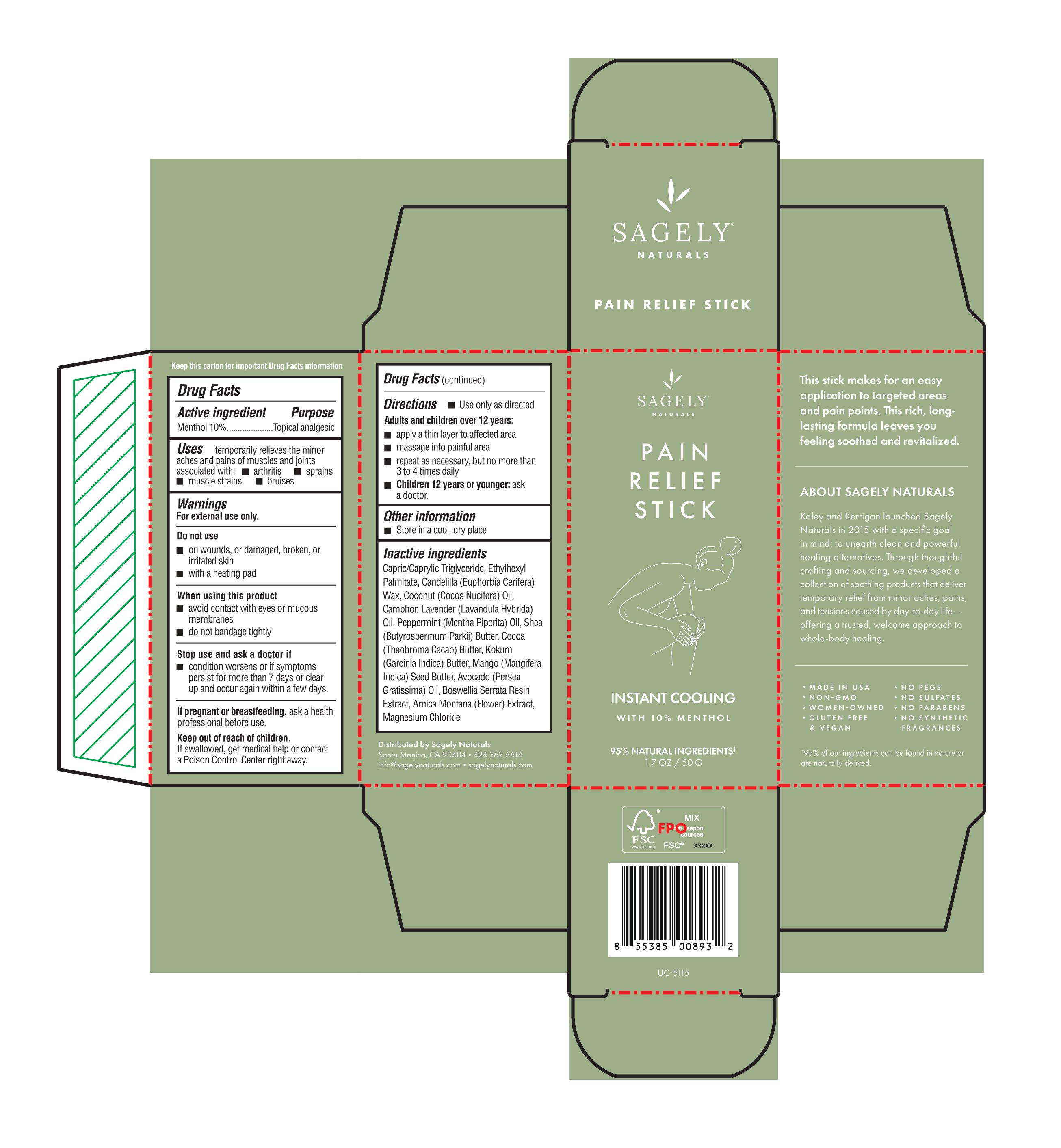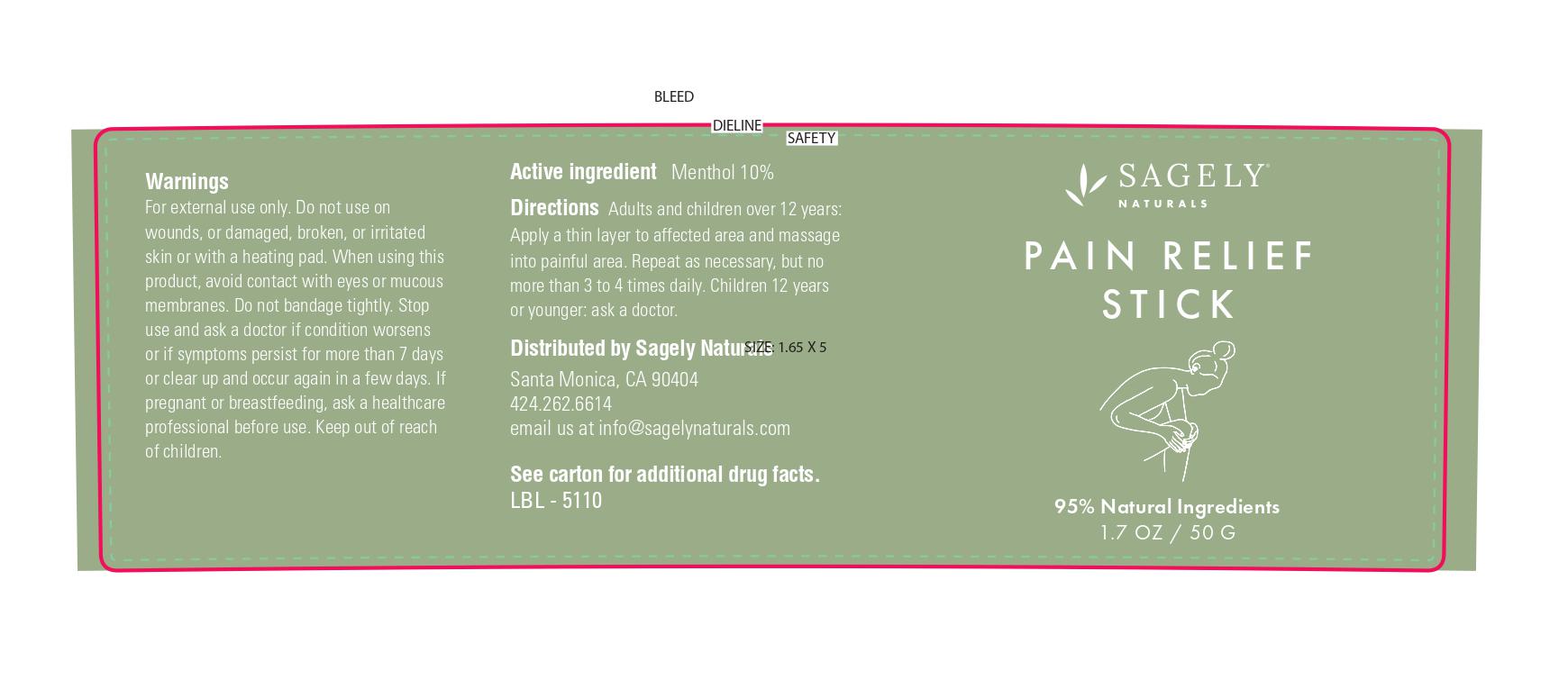 DRUG LABEL: Pain Relief Stick
NDC: 82075-425 | Form: STICK
Manufacturer: Sagely Enterprises Inc.
Category: otc | Type: HUMAN OTC DRUG LABEL
Date: 20210702

ACTIVE INGREDIENTS: MENTHOL 10 g/100 g
INACTIVE INGREDIENTS: PEPPERMINT OIL; GARCINIA INDICA SEED BUTTER; MEDIUM-CHAIN TRIGLYCERIDES; ETHYLHEXYL PALMITATE; COCONUT OIL; CAMPHOR (NATURAL); LAVENDER OIL; MANGIFERA INDICA SEED BUTTER; AVOCADO OIL; CANDELILLA WAX; ARNICA MONTANA; SHEA BUTTER; COCOA BUTTER; BOSWELLIA SERRATA RESIN OIL; MAGNESIUM CHLORIDE

Pain Relief Stick

Active ingredient

Menthol 10%

Purpose

Menthol 10%...................Topical analgesic

Uses

temporarily relieves the minor aches and pains of muscles and joints associated with:

- arthritis
- sprains
- muscle strains
- bruises

Warnings

For external use only.

Do not use

- on wounds, or damaged, broken, or irritated skin
- with a heating pad

When using this product

- avoid contact with eyes or mucous membranes
- do not bandage tightly

Stop use and ask a doctor if

- condition worsens or if symptoms persist for more than 7 days or clear up and occur again within a few days.

PREGNANCY OR BREAST FEEDING

If pregnant or breastfeeding, ask a health professional before use.

Keep out of reach of children. If swallowed, get medical help or contact a Poison Control Center right away.

Directions

- Use only as directed

Adults and children over 12 years:

- apply a thin layer to affected area
- massage into painful area
- repeat as necessary, but no more than 3 to 4 times daily
- Children 12 years or younger: ask a doctor.

Other information

- store in a cool, dry place

Inactive ingredients

Capric/Caprytic Triglyceride, Ethylhexyt Patmttate, Candelilla (Euphorbia Cerifera) WaJI., Coconut (Cocos Nucifera) Oil, Camphor, Lavender (Lavanduta Hybrida) Oil, Peppermint (Mentha Piperita) Oil, Shea (Butyrospermum Parkii) Butter, Cocoa (Theobroma Cacao) Butter, Kokum (Garcinia tndica) Butter, Mango (Mangffera tndica) Seed Butter, Avocado (Persea Gratissima) Oil, Boswellia Serrata Resin Extract, Amica Montana (Flower) Extract, Magnesium Chloride

PACKAGE LABEL

Sagely Naturals

Pain Relief Stick

Instant Cooling

With 10% Menthol

95% Natural Ingredients

1.7 OZ / 50 G